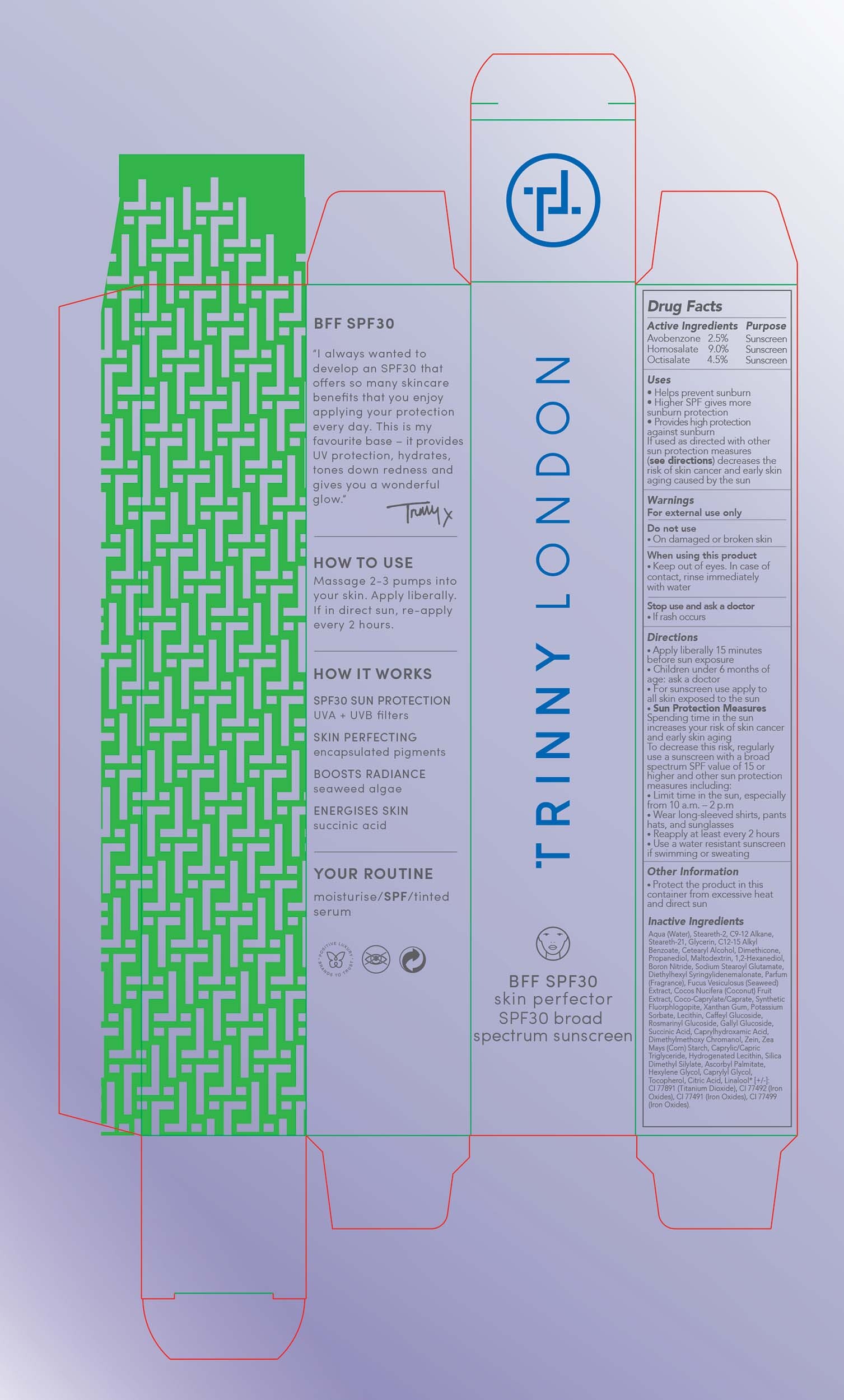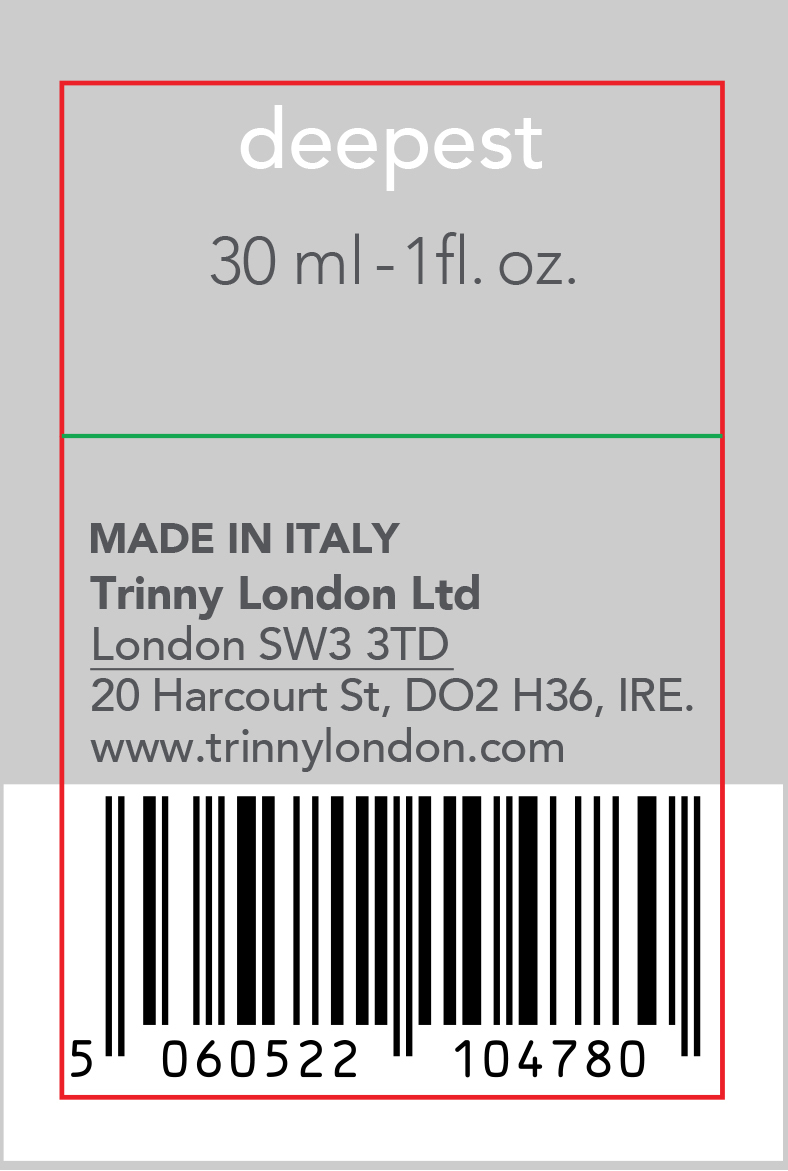 DRUG LABEL: BFF Skin Perfector SPF 30 broad spectrum sunscreen deepest
NDC: 82439-107 | Form: LOTION
Manufacturer: Trinny London Ltd
Category: otc | Type: HUMAN OTC DRUG LABEL
Date: 20220316

ACTIVE INGREDIENTS: HOMOSALATE 9 g/100 mL; OCTISALATE 4.5 g/100 mL; AVOBENZONE 2.5 g/100 mL
INACTIVE INGREDIENTS: POTASSIUM SORBATE; LECITHIN, SUNFLOWER; TOCOPHEROL; FUCUS VESICULOSUS; SUCCINIC ACID; SILICA DIMETHYL SILYLATE; DIETHYLHEXYL SYRINGYLIDENEMALONATE; COCONUT; GLYCERIN; CETOSTEARYL ALCOHOL; 1,2-HEXANEDIOL; BORON NITRIDE; WATER; DIMETHICONE; MALTODEXTRIN; STEARETH-21; SODIUM STEAROYL GLUTAMATE; COCO-CAPRYLATE/CAPRATE; MAGNESIUM POTASSIUM ALUMINOSILICATE FLUORIDE; XANTHAN GUM; ALKYL (C12-15) BENZOATE; PROPANEDIOL; .BETA.-GLUCOGALLIN; ZEIN; MEDIUM-CHAIN TRIGLYCERIDES; HYDROGENATED SOYBEAN LECITHIN; ASCORBYL PALMITATE; CAPRYLYL GLYCOL; CITRIC ACID MONOHYDRATE; STEARETH-2; CAPRYLHYDROXAMIC ACID; HEXYLENE GLYCOL; DIMETHYLMETHOXY CHROMANOL; STARCH, CORN

BFF Skin Perfector SPF 30 broad spectrum sunscreen deepest

Active Ingredients Purpose

Avobenzone 2.5% Sunscreen

Homosalate 9.0% Sunscreen

Octisalate 4.5% Sunscreen

Uses

- Helps prevent Sunburn
- Higher SPF gives more sunburn protection
- Provides high protection against sunburn if used as directed with other sun protection measures (see directions) decreases the risk of skin cancer and early skin aging caused by the sun

Stop use and ask a doctor

- if rash occurs

Warnings

For external use only

Do not use

- On damaged or broken skin

When using this product

- Keep out of eyes. In case of contact, rinse immediately with water

Directions

- Apply Liberally 15 minutes before sun exposure
- Children under 6 months of age: ask a doctor
- For sunscreen use apply to all skin exposed to the sun
- Sun Protection Measures

Spending time in the sun increases your risk of skin cancer and early skin aging. To decrease this risk, regularly use a suncreen with a broad spectrum SPF value of 15 or higher and other sun protection measures including:

- Limit time in the sun, especially from 10 a.m. - 2 p.m.
- Wear long-sleeved shirts, pants, hats and sunglasses
- Reapply at least every 2 hours
- Use a water resistant sunscreen if swimming or sweating

Inactive Ingredients

Aqua (water), Steareth-2, C9-12 Alkane, Steareth-21, Glycerin, C12-15 Alkyl Benzoate, Cetearyl Alcohol, Dimethicone, Propanediol, Maltodextrin, 1,2-Hexanediol, Boron Nitride, Sodium Stearoyl Glutamate, Diethylhexyl Syringylidenemalonate, Parfum (Fragrance), Fucus Vesiculosus (Seaweed) Extract, Cocos Nicifera (Coconut) Fruit Extract, Coco-Caprylate/Caprate, Synthetic Fluorphlogopite, Xanthan Gum, Potassium Sorbate, Lecithin, Caffeyl Glucoside, Rosmarinyl Glucoside, Gallyl Glucoside, Succinic Acid, Caprylhydroxamic Acid, Dimethylmethoxy Chromanol, Zein, Zea Mays (Corn) Starch, Caprylic/Capric Triglyceride, Hydrogenated Lecithin, Silica Dimethyl Silylate, Ascorbyl Palmitate, Hexylene Glycol, Caprylyl Glycol, Tocopherol, Citric Acid, Linalool*[+/-],

CI 77891 (Titanium Dioxide), CI 77492 (Iron Oxides), CI 77491 (Iron Oxides), CI 77499 (Iron Oxides)

Other Information

- Protect the product in this container from excessive heat and direct

PACKAGE LABEL

Trinny London

BFF SPF 30 skin perfector SPF 30 broad spectrum sunscreen

deepest 30 ml - 1 fl. oz.